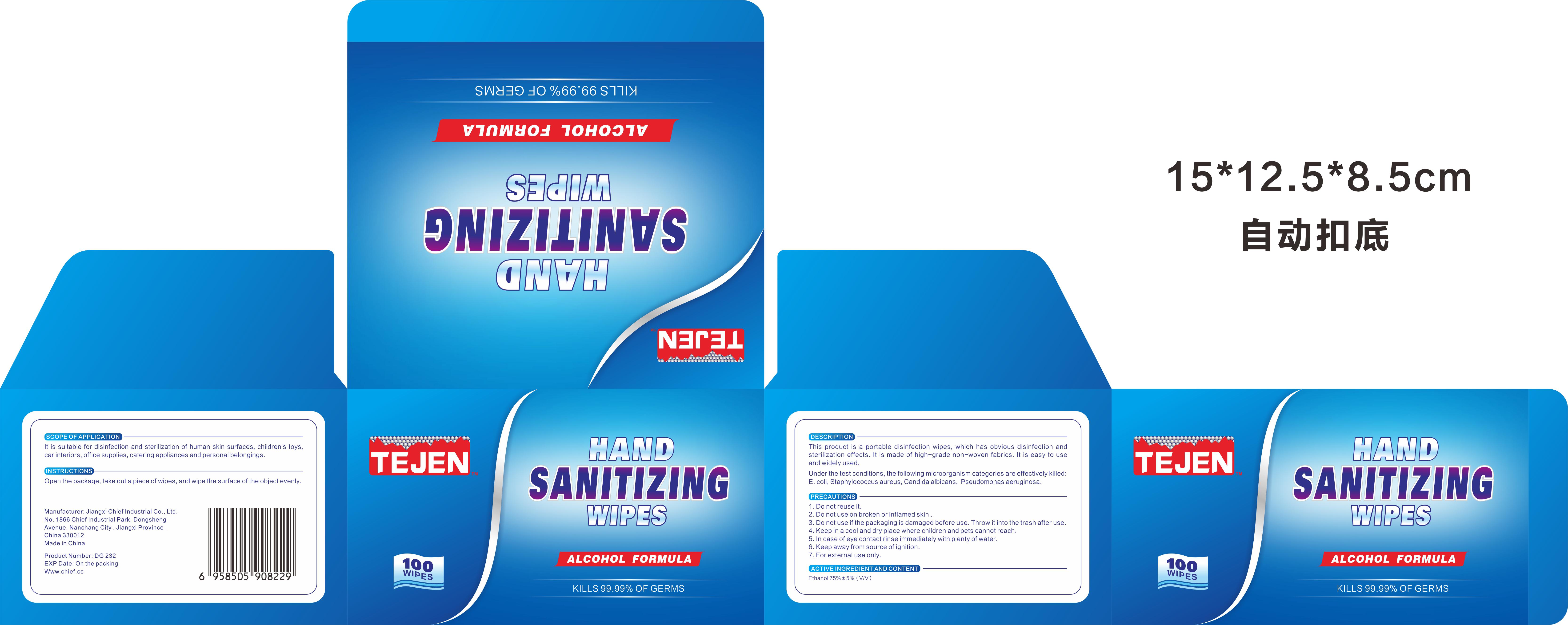 DRUG LABEL: Hand Sanitizing Wipes
NDC: 75524-011 | Form: SWAB
Manufacturer: Jiangxi Chief Industrial Co., Ltd.
Category: otc | Type: HUMAN OTC DRUG LABEL
Date: 20201215

ACTIVE INGREDIENTS: ALCOHOL 75 mL/100 mL
INACTIVE INGREDIENTS: WATER

Hand Sanitizing Wipes

Active Ingredient(s)

Ethanol Alcohol 75%±5% v/v. Purpose: Antibacterial

Purpose

Antibacterial

USE

Decreases bacteria on skin.

Warnings

1. Do not reuse it.

2. Do not use on broken or inflamed skin .

3. Do not use if the packaging is damaged before use. Throw it into the trash after use.

4. Keep in a cool and dry place where children and pets cannot reach.

5. In case of eye contact rinse immediately with plenty of water.

6. Keep away from source of ignition.

7. For external use only.

When using

When using this product keep out of eyes. If contact with eyes occurs, rinse thoroughly with water.

STOP USE

Stop use and ask a doctor if irritation or rash appears and lasts.

Keep out of reach of children. If swallowed, get medical help or contact a Poison Control Center immediately.

Inactive ingredients

Water

Directions

Wet hands thoroughly with product and allow to dry.
Children under 6 years of age should be supervised when using product.

Other information

Do not use or store near heat or flame.

Package Label - Principal Display Panel

100wipes 75524-011-01